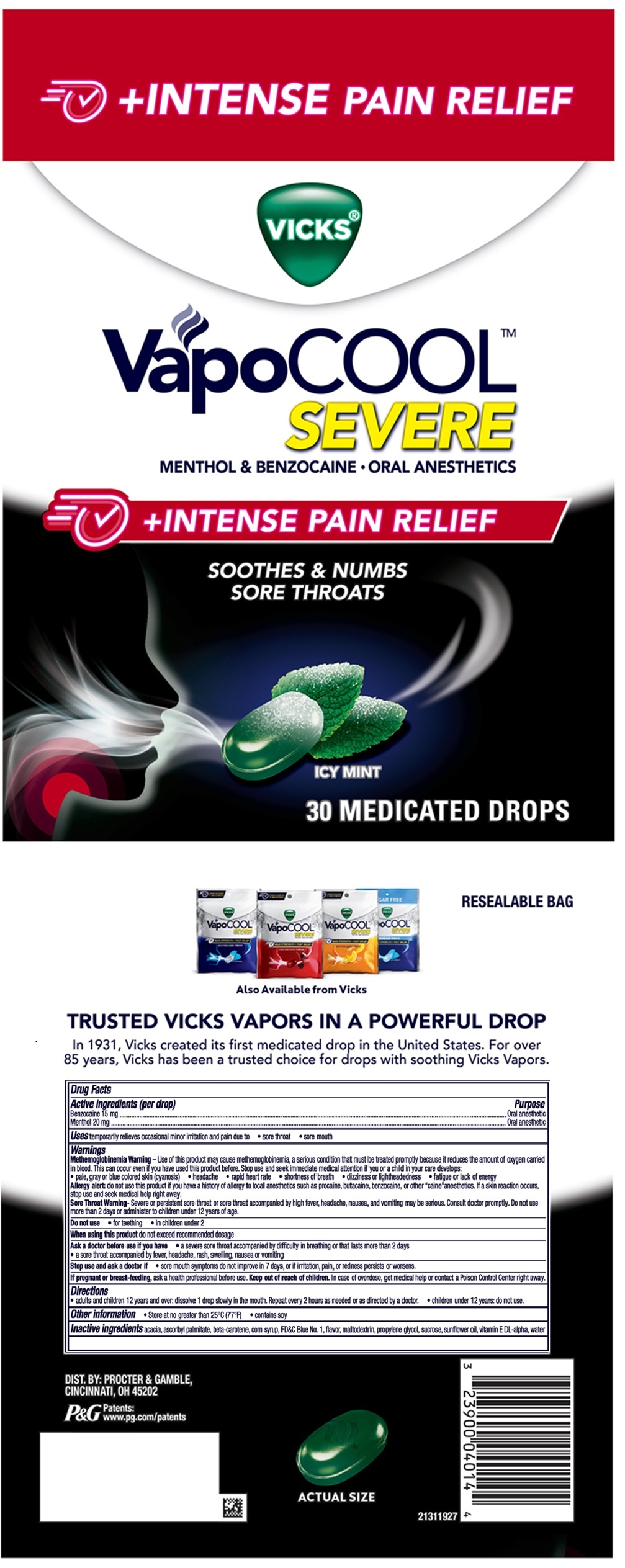 DRUG LABEL: Vicks VapoCool
NDC: 84126-366 | Form: LOZENGE
Manufacturer: The Procter & Gamble Manufacturing Company
Category: otc | Type: HUMAN OTC DRUG LABEL
Date: 20250630

ACTIVE INGREDIENTS: BENZOCAINE 15 mg/1 1; MENTHOL 20 mg/1 1
INACTIVE INGREDIENTS: SUCROSE; CORN SYRUP; PROPYLENE GLYCOL; ASCORBYL PALMITATE; BETA CAROTENE; FD&C BLUE NO. 1; MALTODEXTRIN; SUNFLOWER OIL; .ALPHA.-TOCOPHEROL, DL-; WATER; ACACIA

VICKS® VapoCOOL™ SEVERE + Intense Pain Relief Drops

Drug Facts

Active ingredients (per drop)

Benzocaine 15 mg
Menthol 20 mg

Purpose

Oral anesthetic

Oral anesthetic

Uses

temporarily relieves occasional minor irritation and pain due to

- sore throat
- sore mouth

Warnings

Methemoglobinemia Warning–

Use of this product may cause methemoglobinemia, a serious condition that must be treated promptly because it reduces the amount of oxygen carried in blood. This can occur even if you have used this product before. Stop use and seek immediate medical attention if you or a child in your care develops:

- pale, gray or blue colored skin (cyanosis)
- headache
- rapid heart rate
- shortness of breath
- dizziness or lightheadedness
- fatigue or lack of energy

Allergy alert:

do not use this product if you have a history of allergy to local anesthetics such as procaine, butacaine, benzocaine, or other “caine” anesthetics. If a skin reaction occurs, stop use and seek medical help right away.

Sore Throat Warning –

Severe or persistent sore throat or sore throat accompanied by high fever, headache, nausea, and vomiting may be serious. Consult doctor promptly. Do not use more than 2 days or administer to children under 12 years of age.

Do not use

- for teething
- in children under 2

When using this product

do not exceed recommended dosage

Ask a doctor before use if you have

- a severe sore throat accompanied by difficulty in breathing or that lasts more than 2 days
- a sore throat accompanied by fever, headache, rash, swelling, nausea or vomiting

Stop use and ask a doctor if

- sore mouth symptoms do not improve in 7 days, or if irritation, pain, or redness persists or worsens

PREGNANCY OR BREAST FEEDING

If pregnant or breast-feeding, ask a health professional before use.

Keep out of reach of children.

OVERDOSAGE

In case of overdose, get medical help or contact a Poison Control Center right away.

Directions

- adults and children 12 years and over: dissolve 1 drop slowly in the mouth. Repeat every 2 hours as needed or as directed by a doctor.
- children under 12 years: do not use.

Other information

- Store at no greater than 25°C (77°F)
- contains soy

Inactive ingredients

acacia, ascorbyl palmiltate, beta-carotene, corn syrup, FD&C Blue No. 1, flavor, maltodextrin, propylene glycol, sucrose, sunflower oil, vitamin E DL-alpha, water

Questions?

1-800-707-1709

DIST. BY PROCTER & GAMBLE,
CINCINNATI OH 45202

PRINCIPAL DISPLAY PANEL - 30 MEDICATED DROPS

VICKS ®

VapoCOOL

SEVERE

MENTHOL & BENZOCAINE - ORAL ANESTHETICS

+INTENSE PAIN RELIEF

SOOTHES & NUMBS

SORE THROATS

ICY MINT

30 MEDICATED DROPS